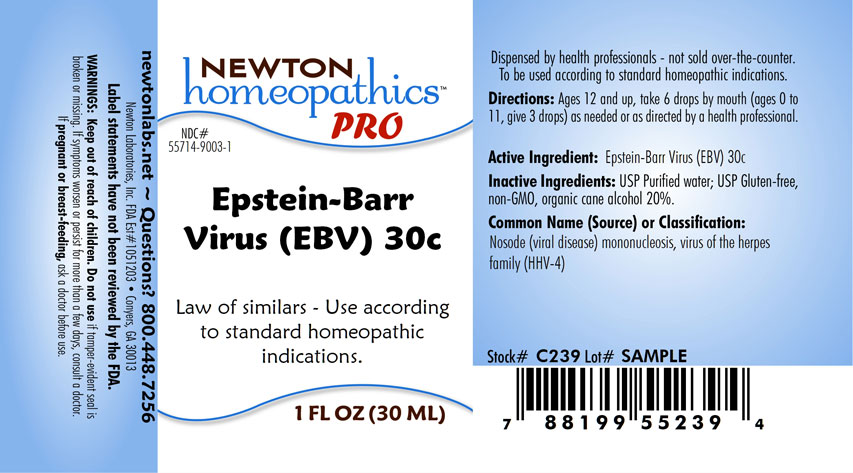 DRUG LABEL: Epstein-Barr Virus
NDC: 55714-9003 | Form: LIQUID
Manufacturer: Newton Laboratories, Inc.
Category: homeopathic | Type: HUMAN OTC DRUG LABEL
Date: 20251223

ACTIVE INGREDIENTS: HUMAN HERPESVIRUS 4 30 [hp_C]/1 mL
INACTIVE INGREDIENTS: ALCOHOL; WATER

Epstein 9003L

INDICATIONS & USAGE SECTION

Law of similars - Use according to standard homeopathic indications.

DOSAGE & ADMINISTRATION SECTION

Directions: Ages 12 and up, take 6 drops by mouth, (Ages 0 to 11, give 3 drops) as needed or as directed by a health professional.

OTC - ACTIVE INGREDIENT SECTION

Epstein-Barr Virus 30c

OTC - PURPOSE SECTION

Law of similars - Use according to standard homeopathic indications.

INACTIVE INGREDIENT SECTION

Inactive Ingredients: USP Purified Water; USP Gluten-free, non-GMO, organic cane alcohol 20%.

QUESTIONS SECTION

newtonlabs.net – Questions? 800.448.7256

Newton Laboratories, Inc. FDA Est # 1051203 - Conyers, GA 30013

WARNINGS SECTION

Warning: Keep out of reach of children. Do not use if tamper - evident seal is broken or missing. If symptoms worsen or persist for more than a few days, consult a doctor. If pregnant or breast-feeding, ask a doctor before use.

OTC - PREGNANCY OR BREAST FEEDING SECTION

If pregnant or breast-feeding, ask a doctor before use.

OTC - KEEP OUT OF REACH OF CHILDREN SECTION

Keep out of reach of children.